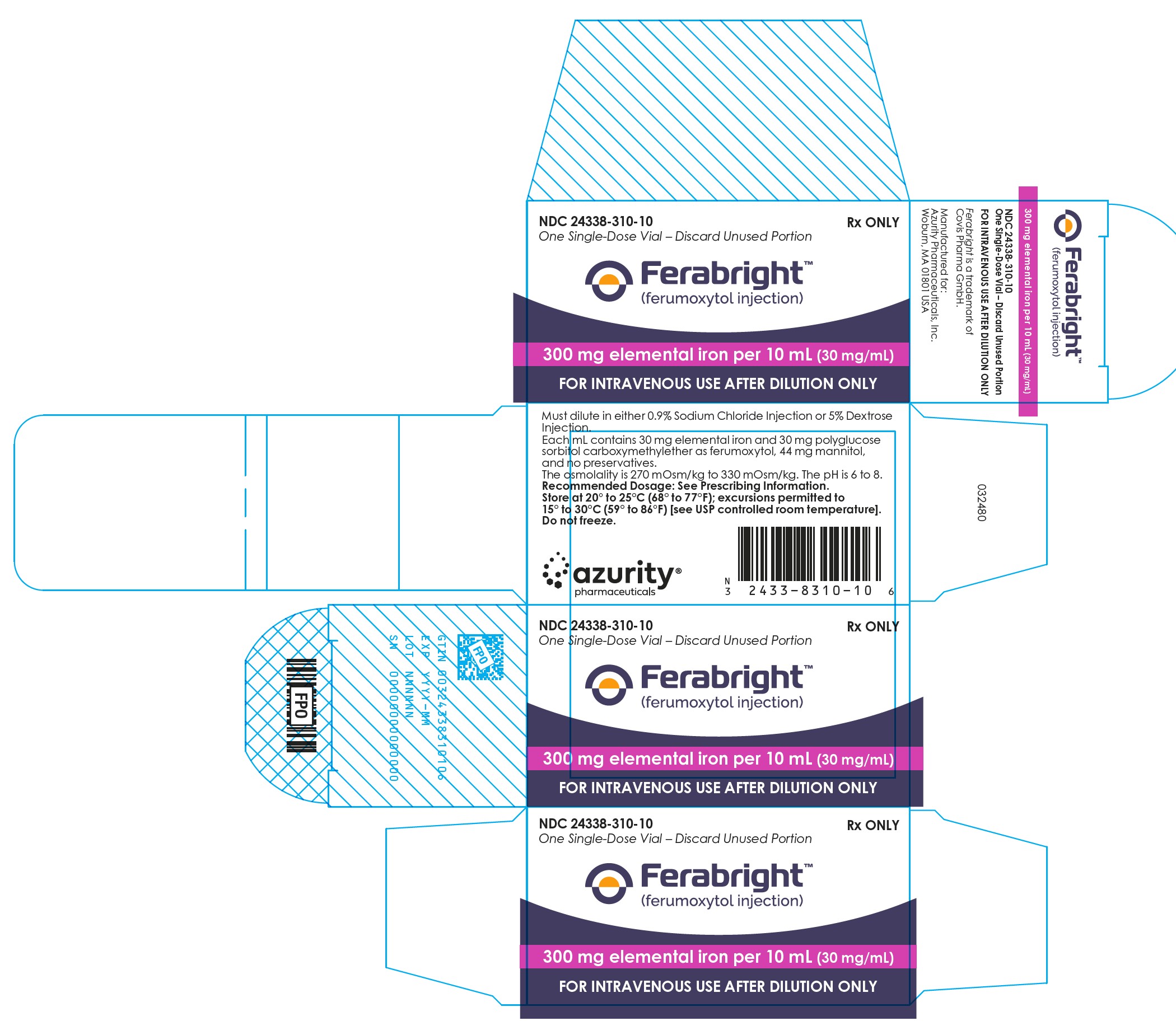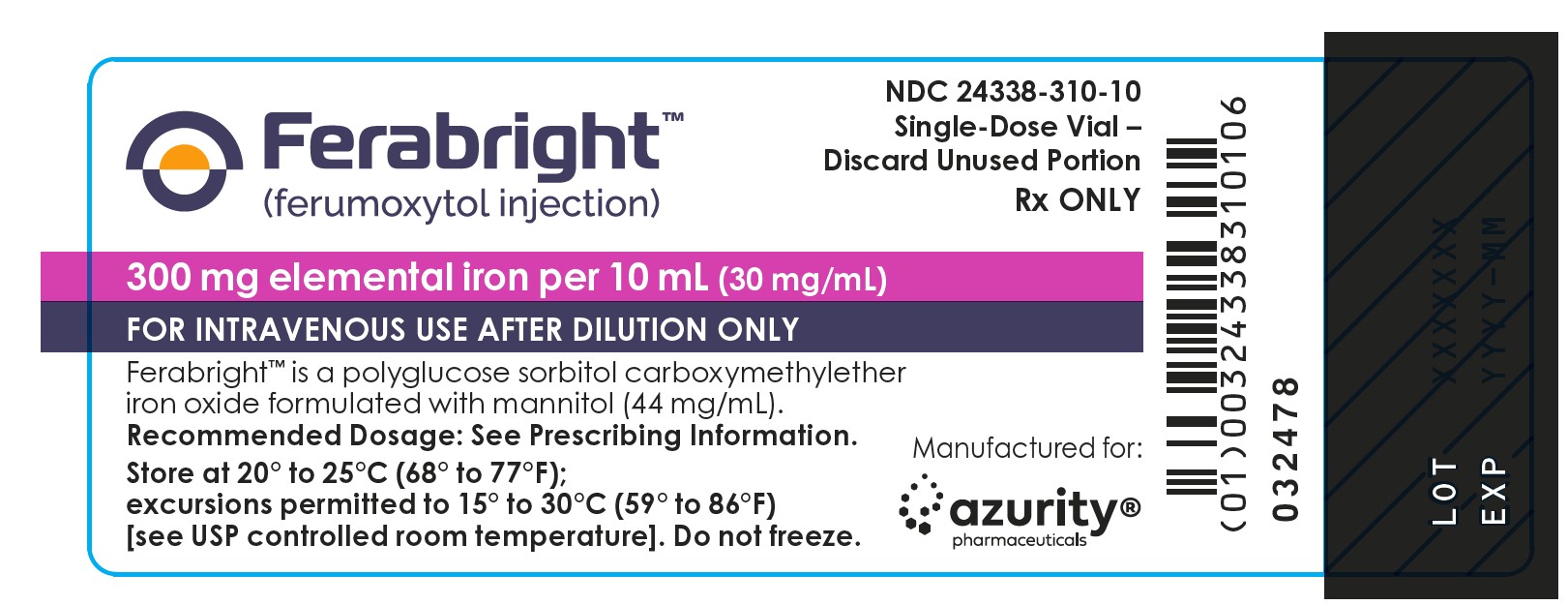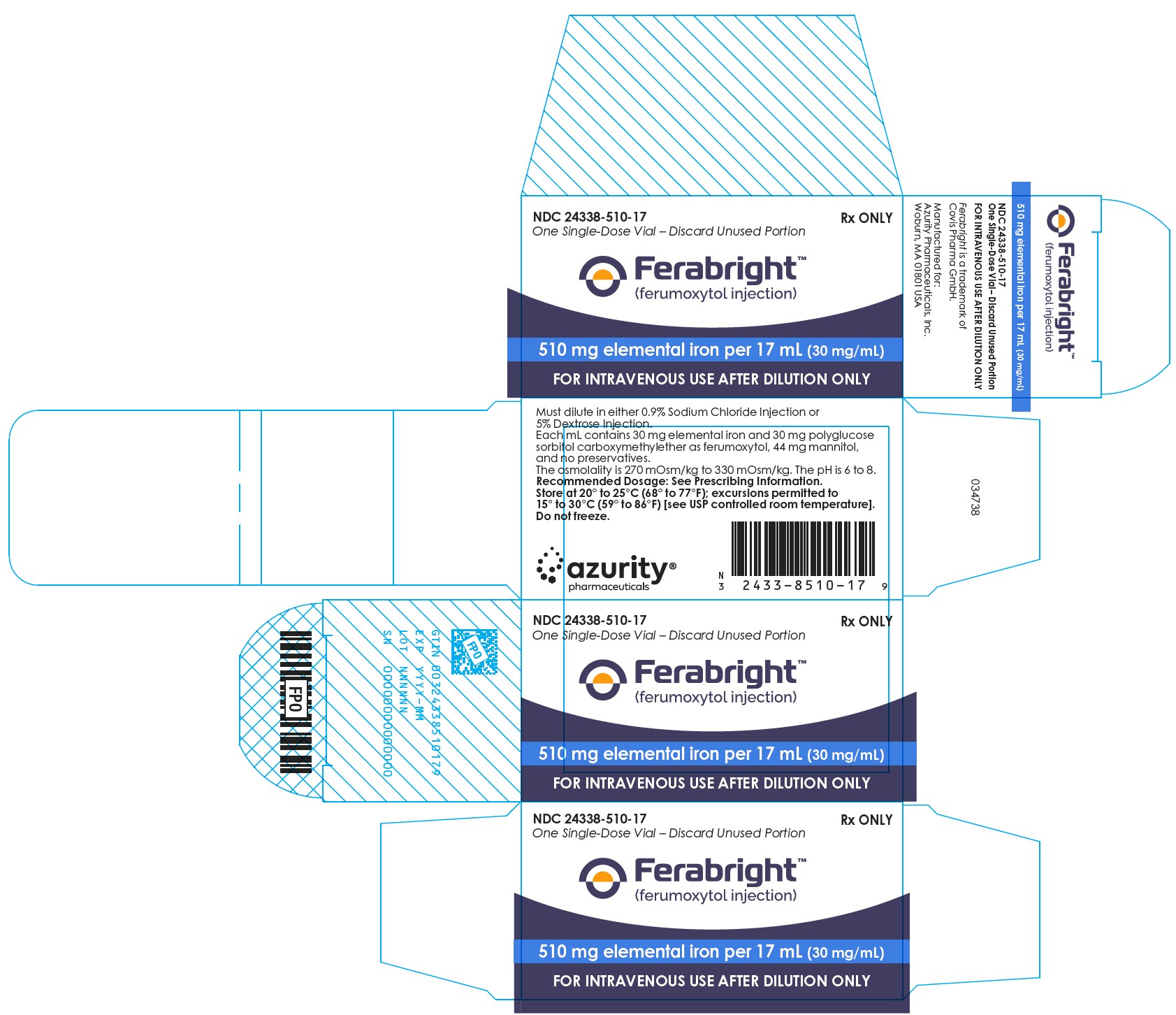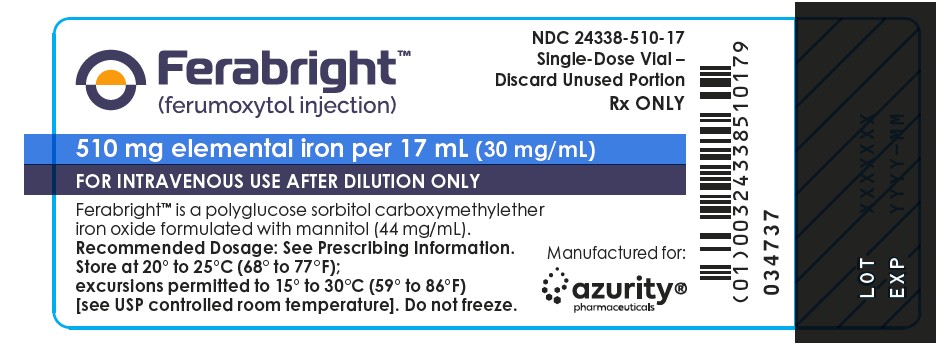 DRUG LABEL: FeraBright
NDC: 24338-310 | Form: INJECTION
Manufacturer: Azurity Pharmaceuticals, Inc.
Category: prescription | Type: Human Prescription Drug Label
Date: 20251014

ACTIVE INGREDIENTS: FERUMOXYTOL 30 mg/1 mL
INACTIVE INGREDIENTS: MANNITOL

HIGHLIGHTS OF PRESCRIBING INFORMATION

These highlights do not include all the information needed to use FERABRIGHT safely and effectively.
See full prescribing information for FERABRIGHT.
FERABRIGHTTM (ferumoxytol injection), for intravenous use
Initial U.S. Approval: 2009

WARNING: ANAPHYLAXIS AND OTHER SERIOUS HYPERSENSITIVITY REACTIONS

Fatal and serious hypersensitivity reactions, including anaphylaxis, have occurred in patients receiving ferumoxytol products that contain the same active ingredient as FERABRIGHT. Initial signs may include hypotension, syncope, unresponsiveness, and cardiac/cardiorespiratory arrest. Hypersensitivity reactions have occurred even in patients who previously tolerated ferumoxytol.

- Only administer FERABRIGHT as an intravenous infusion over at least 15 minutes and only when personnel and therapies are immediately available for the treatment of anaphylaxis and other hypersensitivity reactions.
- Observe for signs or symptoms of hypersensitivity reactions during and for at least 30 minutes following FERABRIGHT infusion including monitoring of blood pressure and pulse during and after FERABRIGHT administration. (5.1)

1 INDICATIONS AND USAGE

FERABRIGHT is an iron-based contrast agent indicated for magnetic resonance imaging (MRI) of the brain in adults with known or suspected malignant neoplasms in the brain to visualize lesions with a disrupted blood-brain barrier.

2 DOSAGE AND ADMINISTRATION

- The recommended dose of FERABRIGHT is based on patient weight:
  - 50 kg or less: 300 mg of elemental iron administered as a single intravenous infusion over at least 15 minutes.
  - 51 kg or more: 510 mg of elemental iron administered as a single intravenous infusion over at least 15 minutes. (2.1)
- FERABRIGHT must be diluted before administration in either 0.9% sodium chloride injection or 5% dextrose injection to achieve concentrations of 2 mg/mL to 8 mg/mL of elemental iron. (2.2)
- Obtain post-contrast T1-weighted images approximately 24 hours after administration. (2.3)

3 DOSAGE FORMS AND STRENGTHS

Injection:

- 300 mg elemental iron per 10 mL (30 mg/mL) in single-dose vials
- 510 mg elemental iron per 17 mL (30 mg/mL) in single-dose vials (3)

4 CONTRAINDICATIONS

- Known hypersensitivity to ferumoxytol, any of FERABRIGHT’s components, or any other intravenous iron products (4)

5 WARNINGS AND PRECAUTIONS

- Hypotension: Monitor for signs and symptoms of hypotension following administration. (5.2)
- Iron Overload: Avoid use of FERABRIGHT in patients with iron overload. (5.3)
- Magnetic Resonance Imaging Test Interference: Conduct anticipated MRI studies (other than the intended FERABRIGHT brain imaging) prior to the administration of FERABRIGHT or use T1- or proton density-weighted pulse sequences if MRI is required within 3 months after administration. (5.4)
- Differences in Magnetic Resonance Imaging Appearance Compared to Gadolinium-Based Contrast: Be aware of the potentially limited interpretability of changes in lesion contrast appearance if prior images were not obtained with FERABRIGHT. (5.5)

6 ADVERSE REACTIONS

The most common adverse reactions (≥0.65%) are nausea, pruritus, constipation, headache, diarrhea, increased blood pressure, bleeding, hyperpigmentation, vein injury, taste alteration, burning/tingling sensation with injection, red sclera, allergic rhinitis, back pain, vomiting, and increased ALT. (6.1)
To report SUSPECTED ADVERSE REACTIONS, contact Azurity Pharmaceuticals, Inc. at 1-800-461-7449, or FDA at 1-800-FDA-1088 or www.fda.gov/medwatch.

FULL PRESCRIBING INFORMATION

WARNING: ANAPHYLAXIS AND OTHER SERIOUS HYPERSENSITIVITY REACTIONS

Fatal and serious hypersensitivity reactions, including anaphylaxis, have occurred in patients receiving ferumoxytol products that contain the same active ingredient as FERABRIGHT. Initial signs may include hypotension, syncope, unresponsiveness, and cardiac/cardiorespiratory arrest. Hypersensitivity reactions have occurred even in patients who previously tolerated ferumoxytol.

- Only administer FERABRIGHT as an intravenous infusion over at least 15 minutes and only when personnel and therapies are immediately available for the treatment of anaphylaxis and other hypersensitivity reactions.
- Observe for signs or symptoms of hypersensitivity reactions during and for at least 30 minutes following FERABRIGHT infusion including monitoring of blood pressure and pulse during and after FERABRIGHT administration [see Warnings and Precautions (5.1)].

1 INDICATIONS AND USAGE

FERABRIGHT is indicated for magnetic resonance imaging (MRI) of the brain in adults with known or suspected malignant neoplasms in the brain to visualize lesions with a disrupted blood-brain barrier.

2 DOSAGE AND ADMINISTRATION

2.1 Recommended Dosage and Administration Instructions

- The recommended dose of FERABRIGHT is based on patient body weight as follows:
  - 50 kg or less: 300 mg of elemental iron diluted in 0.9% sodium chloride injection or 5% dextrose injection [see Dosage and Administration (2.2)].
  - 51 kg or more: 510 mg of elemental iron diluted in 0.9% sodium chloride injection or 5% dextrose injection [see Dosage and Administration (2.2)].
- Administer diluted FERABRIGHT by intravenous infusion over at least 15 minutes while the patient is in a reclined or semi-reclined position approximately 24 hours prior to imaging [see Clinical Pharmacology (12.1)].
- Allow at least 30 minutes after FERABRIGHT infusion for administration of any other medications that may cause serious hypersensitivity reactions or hypotension (e.g., chemotherapeutic agents or monoclonal antibodies) [see Warnings and Precautions (5.1, 5.2)].

2.2 Dilution Instructions

- To achieve a final concentration of 2 mg/mL to 8 mg/mL of elemental iron, add the recommended dose of FERABRIGHT to 0.9% sodium chloride injection or 5% dextrose injection as follows:
  - For a 300 mg dose, add 10 mL of FERABRIGHT to 50 mL to 140 mL diluent.
  - For a 510 mg dose, add 17 mL of FERABRIGHT to 50 mL to 200 mL diluent.
- Inspect diluted FERABRIGHT visually for the absence of particulate matter and discoloration prior to administration.
- Use diluted FERABRIGHT solution immediately. If not used immediately, store the diluted FERABRIGHT solution at controlled room temperature (25°C ± 2°C) for up to 4 hours or refrigerated (2°C to 8°C) for up to 48 hours.
- Each vial of FERABRIGHT is for a single dose. Discard any unused portion.

2.3 Imaging

Obtain post-contrast T1-weighted images approximately 24 hours after FERABRIGHT administration.

3 DOSAGE FORMS AND STRENGTHS

Injection: Black to reddish brown sterile aqueous solution available as:

- 300 mg elemental iron per 10 mL (30 mg/mL) in single-dose vials
- 510 mg elemental iron per 17 mL (30 mg/mL) in single-dose vials

4 CONTRAINDICATIONS

FERABRIGHT is contraindicated in patients with known hypersensitivity to ferumoxytol, any of FERABRIGHT’s components, or any other intravenous iron products. Reactions have included anaphylaxis [see Warnings and Precautions (5.1)].

5 WARNINGS AND PRECAUTIONS

5.1 Anaphylaxis and Other Serious Hypersensitivity Reactions

Fatal and serious hypersensitivity reactions, including anaphylaxis presenting with cardiac/cardiorespiratory arrest, clinically significant hypotension, syncope, or unresponsiveness, have occurred in patients receiving ferumoxytol products, which contain the same active ingredient as FERABRIGHT. Other adverse reactions potentially associated with hypersensitivity have occurred, including pruritus, rash, urticaria, and wheezing. These reactions have occurred in patients who had no prior exposure to ferumoxytol as well as in patients who previously tolerated ferumoxytol.
Patients with a history of multiple drug allergies may have a greater risk of anaphylaxis with FERABRIGHT. Elderly patients with multiple or serious co-morbidities who experience hypersensitivity reactions and/or hypotension following administration of ferumoxytol including FERABRIGHT may have more severe outcomes. Carefully consider the potential risks and benefits before administering FERABRIGHT to these patients. FERABRIGHT is contraindicated in patients with known hypersensitivity to ferumoxytol, any of FERABRIGHT’s components, or any other intravenous iron products [see Contraindications (4)].
Only administer FERABRIGHT as an intravenous infusion over at least 15 minutes and only when personnel and therapies are immediately available for the treatment of anaphylaxis and other hypersensitivity reactions. Closely observe patients for signs and symptoms of hypersensitivity including monitoring of blood pressure and pulse during and after FERABRIGHT administration for at least 30 minutes and until clinically stable following completion of infusion. Allow at least 30 minutes after FERABRIGHT infusion for administration of any other medications that may cause serious hypersensitivity reactions or hypotension [see Dosage and Administration (2.1)].
In a clinical study in patients with iron deficiency anemia (IDA) (FERABRIGHT is not approved to treat IDA), regardless of etiology, hypersensitivity reactions were reported in 0.4% (4/997) of patients administered ferumoxytol as an intravenous infusion over at least 15 minutes. These included one patient with severe hypersensitivity reaction and three patients with moderate hypersensitivity reactions.
In clinical studies predominantly in patients with IDA and chronic kidney disease (CKD) (FERABRIGHT is not approved to treat IDA or CKD), serious hypersensitivity reactions were reported in 0.2% (4/1,806) of patients administered ferumoxytol as a rapid intravenous injection (not an approved method of administration for FERABRIGHT). Other adverse reactions potentially associated with hypersensitivity (e.g., pruritus, rash, urticaria, or wheezing) were reported in 3.5% (63/1,806) of these patients.
In postmarketing experience with ferumoxytol, fatal and serious anaphylactic type reactions presenting with cardiac/cardiorespiratory arrest, clinically significant hypotension, syncope, and unresponsiveness have been reported [see Adverse Reactions (6.2)].

5.2 Hypotension

FERABRIGHT may cause clinically significant hypotension. Monitor patients for signs and symptoms of hypotension following FERABRIGHT administration [see Dosage and Administration (2.1) and Warnings and Precautions (5.1)].
In a clinical study in patients with IDA (FERABRIGHT is not approved to treat IDA), moderate hypotension was reported in 0.2% (2/997) of patients administered ferumoxytol as an intravenous infusion over 15 minutes.
In clinical studies in patients with IDA and CKD (FERABRIGHT is not approved to treat IDA or CKD), hypotension was reported in 1.9% (35/1,806) of patients, including three patients with serious hypotensive reactions, who were administered ferumoxytol as a rapid intravenous injection (not an approved method of administration for FERABRIGHT). Hypotension has also been reported in postmarketing experience [see Adverse Reactions (6.2)].

5.3 Iron overload

Use of FERABRIGHT can lead to excess storage of iron with the possibility of iatrogenic hemosiderosis. Avoid use of FERABRIGHT in patients with iron overload.

5.4 Magnetic Resonance Imaging Test Interference

Administration of FERABRIGHT may transiently affect the diagnostic ability of MRI. Conduct anticipated MRI studies (other than the intended FERABRIGHT brain imaging) prior to the administration of FERABRIGHT. Alteration of MRI studies may persist for up to 3 months following the FERABRIGHT dose. If MRI is required within 3 months after FERABRIGHT administration, use T1- or proton density-weighted pulse sequences to minimize the FERABRIGHT effects. MRI imaging using T2-weighted pulse sequences should not be performed earlier than 4 weeks after the administration of FERABRIGHT. Maximum alteration of vascular MRI signal is evident for 1 to 2 days following FERABRIGHT administration [see Clinical Pharmacology (12.3)].
FERABRIGHT will not interfere with X-ray, computed tomography (CT), positron emission tomography (PET), single photon emission computed tomography (SPECT), planar nuclear medicine imaging, or ultrasound.

5.5 Differences in Magnetic Resonance Imaging Appearance Compared to Gadolinium-Based Contrast

MRI obtained with FERABRIGHT may demonstrate different size, intensity, and pattern of contrast signal in lesions compared to images obtained with gadolinium-based contrast [see Clinical Studies (14)]. Be aware of the potentially limited interpretability of changes in lesion contrast appearance if prior images were not obtained with FERABRIGHT.

6 ADVERSE REACTIONS

The following clinically significant adverse reactions are described elsewhere in the labeling:

- Anaphylaxis and Other Serious Hypersensitivity Reactions [see Warnings and Precautions (5.1)]
- Hypotension [see Warnings and Precautions (5.2)]

6.1 Clinical Trials Experience

Because clinical trials are conducted under widely varying conditions, adverse reaction rates observed in the clinical trials of a drug cannot be directly compared to rates in the clinical trials of another drug and may not reflect the rates observed in practice.
The safety of FERABRIGHT was evaluated in three blinded read studies (Study 001, Study 002, and Study 003) in 225 patients with known or suspected neoplasms in the brain who received FERABRIGHT by intravenous infusion for MRI.
In Study 001, 153 patients weighing between 45 kg and 140 kg received a FERABRIGHT median dose of 506 mg [see Clinical Studies (14)]. The 510 mg dose is recommended in patients weighing 51 kg or more [see Dosage and Administration (2.1)]. The mean (range) age was 52 (18 to 83) years; patients were 57% male, 92% White, 2% Black or African American, 3% Asian, 1% American Indian or Alaska Native, 2% of other race, and 93% Not Hispanic or Latino ethnicity.
In Study 002, 17 patients weighing between 60 kg and 135 kg received a FERABRIGHT median dose of 435 mg. Doses below 510 mg are not recommended in patients weighing 51 kg or more [see Dosage and Administration (2.1)]. The mean (range) age was 52 (32 to 72) years; patients were 65% male, 100% White, and 100% Not Hispanic or Latino ethnicity.
In Study 003, 55 patients weighing between 62 kg and 129 kg received a FERABRIGHT median dose of 312 mg. Doses below 510 mg are not recommended in patients weighing 51 kg or more [see Dosage and Administration (2.1)]. The mean (range) age was 51 (23 to 73) years; patients were 64% male, 91% White, 4% Asian, 2% Native Hawaiian or Other Pacific Islander, 4% of other race, and 93% Not Hispanic or Latino ethnicity.
Adverse reactions reported in patients (≥0.65%) in Study 001 are shown in Table 1.
Table 1: Adverse Reactions Reported in Brain Neoplasm Patients who Received FERABRIGHT for MRI in Study 001*

Adverse Reaction | FERABRIGHT (N = 153) n (%)
Nausea Pruritus Constipation Headache Diarrhea Increased blood pressure Bleeding Hyperpigmentation Vein injury Taste alteration Burning/tingling sensation with injection Red sclera Allergic rhinitis | 3 (1.96%) 2 (1.31%) 2 (1.31%) 1 (0.65%) 1 (0.65%) 1 (0.65%) 1 (0.65%) 1 (0.65%) 1 (0.65%) 1 (0.65%) 1 (0.65%) 1 (0.65%) 1 (0.65%)
*Median dose of 506 mg. The 510 mg dose is recommended in patients weighing 51 kg or more [see Dosage and Administration (2.1)].

Additional adverse reactions reported in Studies 002 and 003 were back pain (3 patients), vomiting (1 patient), and increased ALT (1 patient).

Additional adverse reactions reported in ≥1% of patients with IDA (FERABRIGHT is not approved to treat IDA) in a randomized clinical trial that administered two doses of 510 mg ferumoxytol 3 to 8 days apart by intravenous infusion (not an approved dosing regimen for FERABRIGHT) were dizziness and fatigue.
Additional adverse reactions reported in ≥1% of patients with IDA and CKD (FERABRIGHT is not approved to treat IDA or CKD) in three randomized clinical trials that administered two doses of 510 mg ferumoxytol 3 to 8 days apart by rapid intravenous injection (not an approved dosing regimen for FERABRIGHT) were peripheral edema, edema, abdominal pain, cough, pyrexia, dyspnea, and muscle spasm.

6.2 Postmarketing Experience

The following adverse reactions have been identified during post-approval use of ferumoxytol products, which contain the same active ingredient as FERABRIGHT. Because these reactions are reported voluntarily from a population of uncertain size, it is not always possible to reliably estimate their frequency or establish a causal relationship to drug exposure.
Cardiovascular disorders: cardiac/cardiorespiratory arrest, ischemic myocardial events, acute myocardial ischemia with or without myocardial infarction or with in-stent thrombosis in the context of a hypersensitivity reaction, congestive heart failure, clinically significant hypotension, tachycardia/rhythm abnormalities
General disorders and administration site conditions: cyanosis
Immune system disorders: anaphylaxis and hypersensitivity reactions
Nervous system disorders: syncope, unresponsiveness, loss of consciousness
Skin and system disorders: angioedema
These adverse reactions have usually occurred within 30 minutes after the administration of ferumoxytol.

8 USE IN SPECIFIC POPULATIONS

8.1 Pregnancy

Risk Summary
Limited available data with ferumoxytol use in pregnant women are insufficient to inform a drug associated risk of adverse developmental outcomes. There are risks to the fetus associated with maternal severe hypersensitivity reactions (see Clinical Considerations). In animal studies, administration of ferumoxytol to pregnant rabbits during organogenesis caused adverse developmental outcomes including fetal malformations and decreased fetal weights at maternally toxic doses of 6 times the estimated human daily dose.
The estimated background risk of major birth defects and miscarriage for the indicated populations is unknown. All pregnancies have a background risk of birth defect, loss, or other adverse outcomes. In the U.S. general population, the estimated background risk of major birth defect and miscarriage in clinically recognized pregnancies is 2% to 4% and 15% to 20%, respectively.
Clinical Considerations
Fetal/Neonatal adverse reactions
Severe adverse reactions including circulatory failure (severe hypotension, shock including in the context of anaphylactic reaction) may occur in pregnant women with intravenous iron products (such as FERABRIGHT), which may cause fetal bradycardia, especially during the second and third trimester.
Data
Animal Data
Administration of ferumoxytol during organogenesis, at doses of 31.6 mg Fe/kg/day in rats and 16.5 mg Fe/kg/day in rabbits, did not result in maternal or fetal effects. These doses are approximately 2 times the estimated human daily dose based on body surface area. In rats, administration of ferumoxytol during organogenesis at a maternally toxic dose of 100 mg Fe/kg/day, approximately 6 times the estimated human daily dose based on body surface area, caused a decrease in fetal weights. In rabbits, administration of ferumoxytol during organogenesis at a maternally toxic dose of 45 mg Fe/kg/day, approximately 6 times the estimated human daily dose based on body surface area, was associated with external and soft tissue fetal malformations and decrease in fetal weights.

8.2 Lactation

Risk Summary
There are no data on the presence of ferumoxytol in human milk, the effects on the breastfed child, or the effects on milk production. Ferumoxytol has been detected in the milk of lactating rats. However, due to species-specific differences in lactation physiology, the clinical relevance of these data is not clear. The developmental and health benefits of breastfeeding should be considered along with the mother’s clinical need for FERABRIGHT and any potential adverse effects on the breastfed child from FERABRIGHT or from the underlying maternal condition.

8.4 Pediatric Use

The safety and effectiveness of FERABRIGHT in pediatric patients (less than 18 years old) have not been established.

8.5 Geriatric Use

Of the total number of patients administered FERABRIGHT in the brain MRI re-read studies, 40 (18%) were 65 years of age and older, and 8 (4%) were 75 years of age and older [see Adverse Reactions (6.1)]. No overall differences in safety or effectiveness were observed between these patients and younger patients, and other reported clinical experience has not identified differences between the elderly and younger patients.
Elderly patients with multiple or serious co-morbidities who experience hypersensitivity reactions and/or hypotension following administration of FERABRIGHT may have more severe outcomes. In general, dose administration to an elderly patient should be cautious, reflecting the greater frequency of decreased hepatic, renal, or cardiac function, and of concomitant disease or other drug therapy [see Warnings and Precautions (5.1)].

10 OVERDOSAGE

Excessive dosages of FERABRIGHT may lead to accumulation of iron in storage sites potentially leading to hemosiderosis [see Warnings and Precautions (5.3)].
Ferumoxytol is not removed by hemodialysis.

11 DESCRIPTION

FERABRIGHT (ferumoxytol injection) is an iron-based contrast agent for intravenous use.
Ferumoxytol is a non-stoichiometric magnetite (superparamagnetic iron oxide) coated with polyglucose sorbitol carboxymethylether. The overall colloidal particle size ranges from 31 nm to 43 nm in diameter. The chemical formula of ferumoxytol is Fe5874O8752-C11719H18682O9933Na414 with an apparent molecular weight of 750 kDa.
Each mL contains 30 mg of elemental iron and 30 mg of polyglucose sorbitol carboxymethylether as ferumoxytol, and 44 mg of mannitol. It contains no preservatives.
FERABRIGHT is a sterile, aqueous, black to reddish brown, isotonic colloidal solution with an osmolality of 270 mOsm/kg to 330 mOsm/kg, magnetic susceptibility of 27,250 to 39,000 x 10^-6 cgs/g Fe, and a pH of 6 to 8.

12 CLINICAL PHARMACOLOGY

12.1 Mechanism of Action

Ferumoxytol is a superparamagnetic iron oxide coated with a carbohydrate shell that develops a magnetic moment when placed in a magnetic field. The magnetic moment alters the relaxation rates of water protons in its vicinity in the body, leading to an increase in signal intensity (brightness) of tissues on T1-weighted MRI. Disruption of the blood-brain barrier allows distribution of ferumoxytol into lesions such as neoplasms. Since extravasation of the large ferumoxytol molecules is slow, parenchymal enhancement is seen in the delayed phase, approximately 24 hours post-administration of FERABRIGHT.

12.2 Pharmacodynamics

Ferumoxytol exposure-response relationships and the time course of pharmacodynamic response are unknown.
Cardiac Electrophysiology
In a randomized, positive- and placebo-controlled, parallel-group study, healthy subjects received rapid intravenous injection of two 510 mg doses of ferumoxytol within 24 hours (not an approved dosing regimen for FERABRIGHT), placebo, or a single dose of 400 mg moxifloxacin (positive control). Results demonstrated no effect of ferumoxytol on QT interval durations. No clinically meaningful effect of ferumoxytol on heart rate was observed.

12.3 Pharmacokinetics

Ferumoxytol maximum concentration (Cmax) increases proportionally and area under the concentration-time curve (AUC) increases more than proportionally over a dose range from 1 mg/kg (70 mg in a patient with body weight of 70 kg- not an approved dosing regimen for FERABRIGHT) to 510 mg elemental iron. Rate of infusion ranging from 2 mL/min to 60 mL/min has no significant influence on pharmacokinetics (PK) of ferumoxytol.
Distribution
The volume of distribution is 3.4 L.
Elimination
Ferumoxytol exhibits dose-dependent, capacity-limited elimination from plasma. Terminal half-life increases by increasing the dose of ferumoxytol. Terminal half-life is approximately 21 hours after a single 510 mg elemental iron dose.
Specific Populations
Ferumoxytol clearance increases with body weight. There are no clinically significant differences in the PK of ferumoxytol based on age (18 to 77 years), sex, race (Black or White), or renal function (CLcr: 4.9 to 188 mL/min).

13 NONCLINICAL TOXICOLOGY

13.1 Carcinogenesis, Mutagenesis, Impairment of Fertility

Carcinogenesis
Ferumoxytol was not tested for carcinogenic effects.
Mutagenesis
In standard genotoxicity tests, ferumoxytol showed no evidence of mutagenic activity in an in vitro Ames test or clastogenic activity in either an in vitro chromosomal aberration assay or an in vivo micronucleus assay.
Impairment of Fertility
Ferumoxytol had no effect on male or female fertility or general reproductive function in rats.
In a prenatal and postnatal development study in rats, intravenous administration of ferumoxytol from gestation day 6 until lactation day 20 at doses up to 60 mg Fe/kg/day (approximately 3 times the daily human dose based on body surface area comparisons assuming a 60-kg person) had no effect on maternal delivery or numbers of liveborn offspring. Male offspring (F1) of pregnant rats (F0) administered ferumoxytol at a dose of 60 mg Fe/kg/day had delayed sexual maturation and decreased reproductive competence. Female offspring (F1) of pregnant rats (F0) administered ferumoxytol at doses of 30 mg Fe/kg/day or 60 mg Fe/kg/day had delayed sexual maturation and decreased reproductive competence. Doses of 30 mg Fe/kg/day and 60 mg Fe/kg/day are approximately 2 and 3 times the daily human dose based on body surface area comparisons assuming a 60-kg person, respectively.

14 CLINICAL STUDIES

The effectiveness of FERABRIGHT for intra-axial malignant brain lesion visualization was evaluated in a blinded read study of MRIs acquired from one open-label, intra-patient controlled clinical trial. The trial enrolled adult patients with known or suspected primary and secondary intra-axial neoplasms in the brain. Each patient received MRI before and after intravenous administration of an approved gadolinium-based contrast agent. Within seven days, MRI was performed before and after administration of a single dose of FERABRIGHT. Images from a total of 153 patients with known or suspected primary and secondary malignant intra-axial neoplasms in the brain who received approximately 510 mg of FERABRIGHT were analyzed in the blinded read study.
The mean age and weight of the 153 patients in the study were 52 years (range 18 to 83 years) and 83 kg, respectively. Patients were 57% male, 92% White, 2% Black or African American, 3% Asian, 1% American Indian or Alaska Native, 2% of other race, and 93% Not Hispanic or Latino ethnicity.
Pre-contrast and combined pre-contrast and post-contrast image sets were separately evaluated by three independent readers who were blinded to patient information and contrast agent. The FERABRIGHT combined pre-contrast and post-contrast image set consisted of T1-weighted sequences in the 24-hour delayed phase plus the pre-contrast images obtained prior to FERABRIGHT administration. Each reader scored up to five lesions measuring at least 1 cm in diameter for visualization parameters of contrast enhancement, border delineation, and internal morphology. Each parameter was scored on a four-point scale. The total number of lesions visualized per patient was also reported. An additional independent central reader performed lesion tracking to allow matching of lesions between pre-contrast and combined image sets. The primary analysis compared the patient-level average score for each visualization parameter in matching lesions between pre-contrast and combined image sets.
Results of the primary analysis of per-reader lesion visualization parameter scoring for pre-FERABRIGHT and combined pre- and post-FERABRIGHT images are shown in Table 2.

Table 2: Patient-Level Lesion Visualization Scores by Reader for Combined and Pre-Contrast MRI in Patients Receiving FERABRIGHT

 |  | LS Mean (SE) |  |  | 95% CI Difference
Parameter | n | Combined | Pre | Difference* | 95% CI Difference
Contrast enhancement
Reader 1 | 116 | 3.1 (0.06) | 1.0 (0.06) | 2.1 (0.09) | (1.9, 2.2)
Reader 2 | 126 | 3.1 (0.07) | 1.0 (0.07) | 2.1 (0.10) | (1.9, 2.3)
Reader 3 | 138 | 2.6 (0.07) | 1.0 (0.07) | 1.6 (0.09) | (1.4, 1.8)
Border delineation
Reader 1 | 116 | 3.0 (0.07) | 1.6 (0.07) | 1.4 (0.09) | (1.2, 1.6)
Reader 2 | 126 | 3.1 (0.08) | 1.8 (0.08) | 1.2 (0.10) | (1.1, 1.4)
Reader 3 | 138 | 3.1 (0.06) | 2.6 (0.06) | 0.5 (0.08) | (0.4, 0.7)
Internal morphology
Reader 1 | 116 | 3.1 (0.07) | 1.6 (0.07) | 1.4 (0.09) | (1.2, 1.6)
Reader 2 | 126 | 2.9 (0.08) | 1.7 (0.08) | 1.2 (0.11) | (1.0, 1.5)
Reader 3 | 138 | 2.4 (0.07) | 1.9 (0.07) | 0.5 (0.09) | (0.3, 0.7)
Only matching lesions were considered. The mixed-effects models were based on the enrolled patients with pre- and post-FERABRIGHT images (n=152). The models included lesion visualization parameter as a dependent variable, MRI type (combined vs. pre-contrast) as a fixed effect, and patient as a random effect. Under this model and the paired design, SEs for the LS-means are expected to be equal.
Abbreviations: CI = confidence interval; LS = least squares; SE = standard errors.
*p<0.0001 for all rows

FERABRIGHT lesion visualization scores and number of lesions visualized per patient were similar to those of comparator gadolinium-based contrast agents. In a side-by-side comparison of post-contrast T1-weighted images, some patients were rated as having larger or smaller size, greater or lesser intensity, and different pattern of lesion contrast between FERABRIGHT and gadolinium-based contrast [see Warnings and Precautions (5.5)].

16 HOW SUPPLIED/STORAGE AND HANDLING

How Supplied
FERABRIGHT (ferumoxytol injection) is a black to reddish brown, sterile aqueous solution available as:

Total Amount per Total Volume (Concentration) | Package Type | Vials per Carton | NDC
300 mg elemental iron per 10 mL (30 mg/mL) | Single-Dose Vial | One | 24338-310-10
510 mg elemental iron per 17 mL (30 mg/mL) | Single-Dose Vial | One | 24338-510-17

Storage and Handling

Store at 20°C to 25°C (68°F to 77°F). Excursions permitted to 15°C to 30°C (59°F to 86°F) [see USP controlled room temperature]. Do not freeze.

17 PATIENT COUNSELING INFORMATION

Advise the patient to read the FDA-approved patient labeling (Patient Information).
Anaphylaxis and Other Serious Hypersensitivity Reactions
Inform patients of the risk of hypersensitivity reactions, including anaphylaxis. Discuss with patients regarding any prior history of allergies to intravenous iron products, and advise them to immediately report any symptoms of hypersensitivity that may develop during and following FERABRIGHT administration, such as rash, itching, dizziness, light-headedness, swelling, and breathing problems [see Contraindications (4) and Warnings and Precautions (5.1)].
Manufactured for:
Azurity Pharmaceuticals, Inc.
Woburn, MA 01801 USA

Patient Package Insert

PATIENT INFORMATION
FERABRIGHTTM (FAYR-a-brite)
(ferumoxytol injection)
for intravenous use

What is the most important information I should know about FERABRIGHT?
FERABRIGHT can cause serious side effects, including:

- Serious allergic reactions that can lead to death. Serious allergic reactions have happened in people receiving ferumoxytol products such as FERABRIGHT. Even if you have received ferumoxytol before without any problems, you could still develop an allergic reaction with a future dose. If you have a history of allergies to many different medicines, you may have an increased risk of serious allergic reactions to FERABRIGHT. Immediately tell your healthcare provider or get medical help right away if you get any of these signs or symptoms:
  - rash
  - itching
  - dizziness or lightheadedness
  - low blood pressure
  - swelling of the tongue or throat
  - wheezing or trouble breathing
  - feeling faint or fainting (syncope)

See “What are the possible side effects of FERABRIGHT?” for more information about side effects.

What is FERABRIGHT?
FERABRIGHT is an iron-based dye for brain magnetic resonance imaging (MRI) scans in adults who have or may have brain cancer. It helps healthcare providers see malignant tumors that have disrupted the protective barrier around the brain (blood-brain barrier).
It is not known if FERABRIGHT is safe and effective in children less than 18 years of age.

Who should not receive FERABRIGHT?
Do not receive FERABRIGHT if you:

- are allergic to ferumoxytol or any of the ingredients in FERABRIGHT. See the end of this leaflet for a complete list of ingredients in FERABRIGHT.
- have had an allergic reaction to any iron medicine given into your vein by intravenous (IV) infusion.

Before receiving FERABRIGHT, tell your healthcare provider about all of your medical conditions, including if you:

- have allergies to many different medicines
- have low blood pressure (hypotension)
- have too much iron stored in your body (iron overload)
- are pregnant or plan to become pregnant. Your unborn baby may be harmed if you experience a severe allergic reaction to FERABRIGHT.
- are breastfeeding or plan to breastfeed. It is not known if FERABRIGHT passes into breast milk.

Tell your healthcare provider about all the medicines you take, including prescription and over-the-counter medicines, vitamins, and herbal supplements.

How will I receive FERABRIGHT?

- Your healthcare provider will advise you when you need to be administered the dose of FERABRIGHT and when your MRI scan will occur.
- FERABRIGHT will be given to you into your vein by intravenous (IV) infusion over at least 15 minutes by your healthcare provider about 24 hours before your MRI scan. You may also have an MRI scan before the FERABRIGHT infusion.
- You will be positioned partially or completely laying back with your back supported while receiving FERABRIGHT.
- Your healthcare provider will watch you during and for at least 30 minutes after you receive FERABRIGHT.
- Wait at least 30 minutes after FERABRIGHT infusion before receiving other medicines that may cause allergic reactions or low blood pressure such as chemotherapy or antibody treatment.

What are the possible side effects of FERABRIGHT?
FERABRIGHT can cause serious side effects, including:

- See “What is the most important information I should know about FERABRIGHT?”
- Low blood pressure (hypotension) is a side effect of FERABRIGHT that can sometimes be serious. Your healthcare provider will check you for signs and symptoms of hypotension after each FERABRIGHT infusion. Report the following symptoms immediately to your healthcare provider:
  - feeling dizzy or lightheaded
  - feeling faint or fainting (syncope)
  - blurred vision
  - trouble concentrating or confused
  - feeling weak, tired, or sleepy
  - upset stomach or vomiting
- Iron overload. FERABRIGHT can cause too much iron storage in your body.
- MRI Test Interference. Tell your healthcare provider if you have any MRIs, other than your brain scan, scheduled in the next 3 months after you receive FERABRIGHT, because it may affect the test results.

The most common side effects of FERABRIGHT include:

- nausea
- itchy skin (pruritus)
- constipation
- headache
- diarrhea
- high blood pressure
- bleeding
- skin darkening (hyperpigmentation)
- blood vessel injury
- change in taste
- burning or tingling with injection
- red eyes (red sclera)
- stuffy or runny nose
- back pain
- vomiting
- increase in blood liver enzymes

These are not all of the possible side effects of FERABRIGHT. Call your doctor for medical advice about side effects. You may report side effects to FDA at 1-800-FDA-1088.

General information about the safe and effective use of FERABRIGHT.
Medicines are sometimes prescribed for purposes other than those listed in a Patient Information leaflet. If you would like more information, talk to your healthcare provider. You can ask your pharmacist or healthcare provider for information about FERABRIGHT that is written for healthcare professionals.

What are the ingredients in FERABRIGHT?
Active ingredient: ferumoxytol
Inactive ingredient: mannitol
Manufactured for:
Azurity Pharmaceuticals, Inc.,
Woburn, MA 01801 USA
For more information, go to www.ferabright.com or call 1-800-461-7449.

This Patient Information has been approved by the U.S. Food and Drug Administration. Approved: 10/2025

PRINCIPAL DISPLAY PANEL – 10 mL

NDC 24338-310-10 Rx ONLY
One Single-Dose Vial – Discard Unused Portion

FerabrightTM
(ferumoxytol injection)

300 mg elemental iron per 10 mL (30 mg/mL)

FOR INTRAVENOUS USE AFTER DILUTION ONLY

NDC 24338-310-10 Rx ONLY
Single-Dose Vial – Discard Unused Portion

FerabrightTM
(ferumoxytol injection)

300 mg elemental iron per 10 mL (30 mg/mL)

FOR INTRAVENOUS USE AFTER DILUTION ONLY

PRINCIPAL DISPLAY PANEL – 17 mL

NDC 24338-510-17 Rx ONLY
One Single-Dose Vial – Discard Unused Portion

FerabrightTM
(ferumoxytol injection)

510 mg elemental iron per 17 mL (30 mg/mL)

FOR INTRAVENOUS USE AFTER DILUTION ONLY

NDC 24338-510-17 Rx ONLY
Single-Dose Vial – Discard Unused Portion

FerabrightTM
(ferumoxytol injection)

510 mg elemental iron per 17 mL (30 mg/mL)

FOR INTRAVENOUS USE AFTER DILUTION ONLY